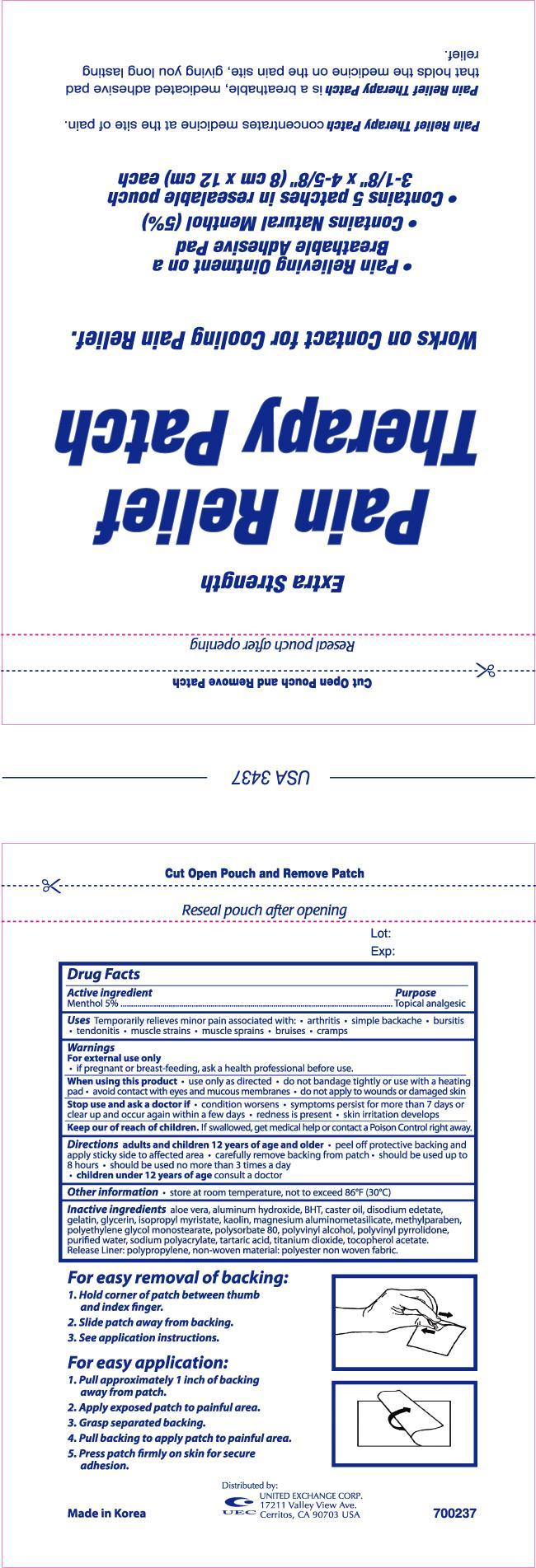 DRUG LABEL: PAIN RELIEF THERAPY PATCH
                
NDC: 65923-700 | Form: PATCH
Manufacturer: UNITED EXCHANGE CORP
Category: otc | Type: HUMAN OTC DRUG LABEL
Date: 20130131

ACTIVE INGREDIENTS: MENTHOL 750 mg/1 1
INACTIVE INGREDIENTS: ALUMINUM HYDROXIDE; EDETATE DISODIUM; GELATIN; KAOLIN; METHYLPARABEN; GLYCERIN; TITANIUM DIOXIDE; ISOPROPYL MYRISTATE; WATER

Drug Facts

Active ingredient Purpose

Menthol 5% .....................................................................Topical analgesic

PURPOSE

Uses temporarily relieves minor pain associated with:

- arthritis
- simple backache
- bursitis
- tendonitis
- muscle strains
- muscle sprains
- bruises
- cramps

Warnings

For external use only

When using this product:

- use only as directed
- do not bandage tightly or use with heating pad
- avoid contact with eyes and mucous membranes
- do not apply to wounds or damaged skin

Stop use and ask a doctor if:

- condition worsens
- symptoms persist for more than 7 days or clear up and occur again within a few days
- redness is present
- skin irritation develops

PREGNANCY OR BREAST FEEDING

If pregnant or breast-feeding, ask a health professional before use.

Keep out of reach of children. If swallowed, get medical help or contact a Poison Control Center right away.

Directions

adults and children 12 years of age and older:

- peel off protective backing and apply sticky side to affected area
- carefully remove backing from patch
- should be used up to 8 hours
- should be used no more than 3 times a day

children under 12 years of age:

- consult a doctor

INACTIVE INGREDIENT

Inactive ingredients: Aloe Barbadensis Leaf Juice, Aluminum Hydroxide, Disodium EDTA, Gelatin, Kaolin, Methylparaben, Glycerin, Titanium Dioxide, Isopropyl Myristate, Purified Water,

Polyvinyl Pyrrolidone, Peg-4 Stearate, Polyvinyl Alcohol, Polysorbate 80, PVP, Tocopherol Acetate, Alumino Magnesium Metasilicate, Castor Oil, Tartaric Acid, BHT, Sodium Polyacrylate.

DOSAGE AND ADMINISTRATION

Distributed by:

UNITED EXCHANGE CORP

17211 Valley View Ave.

Cerritos, CA 90703 USA

MADE IN KOREA